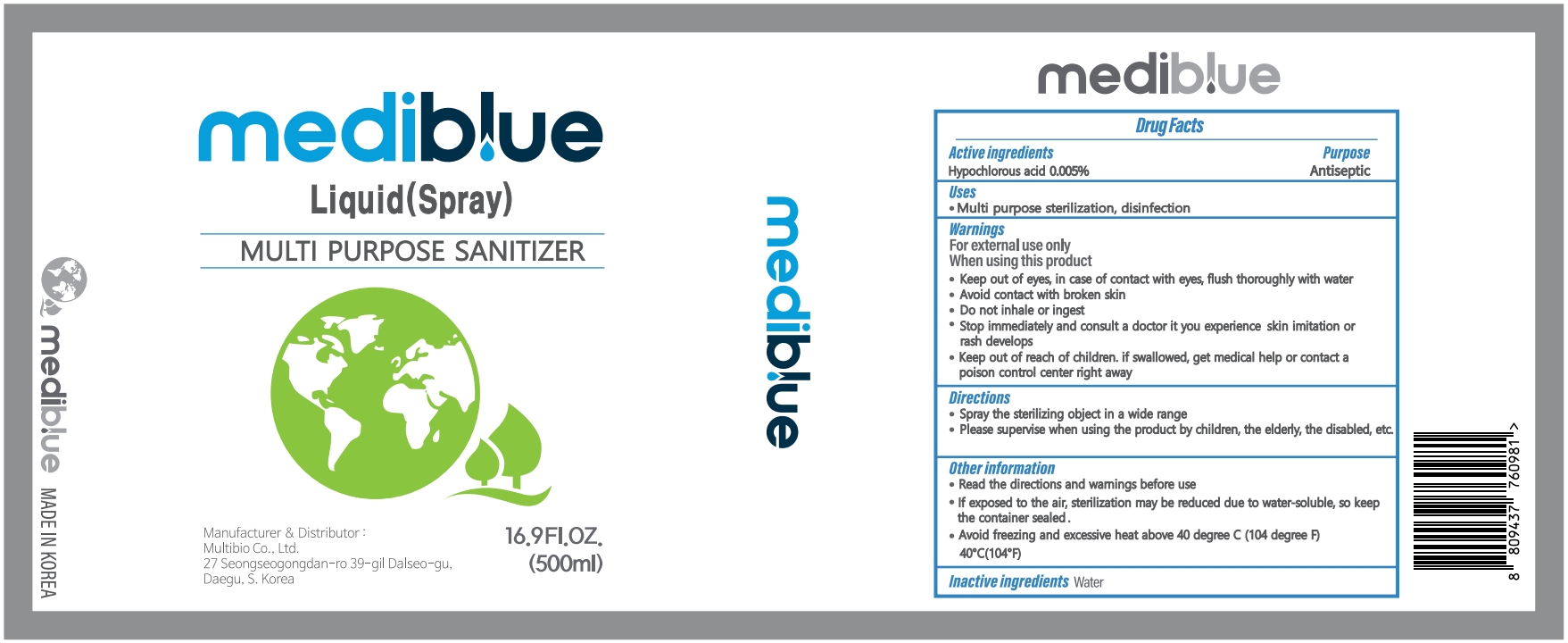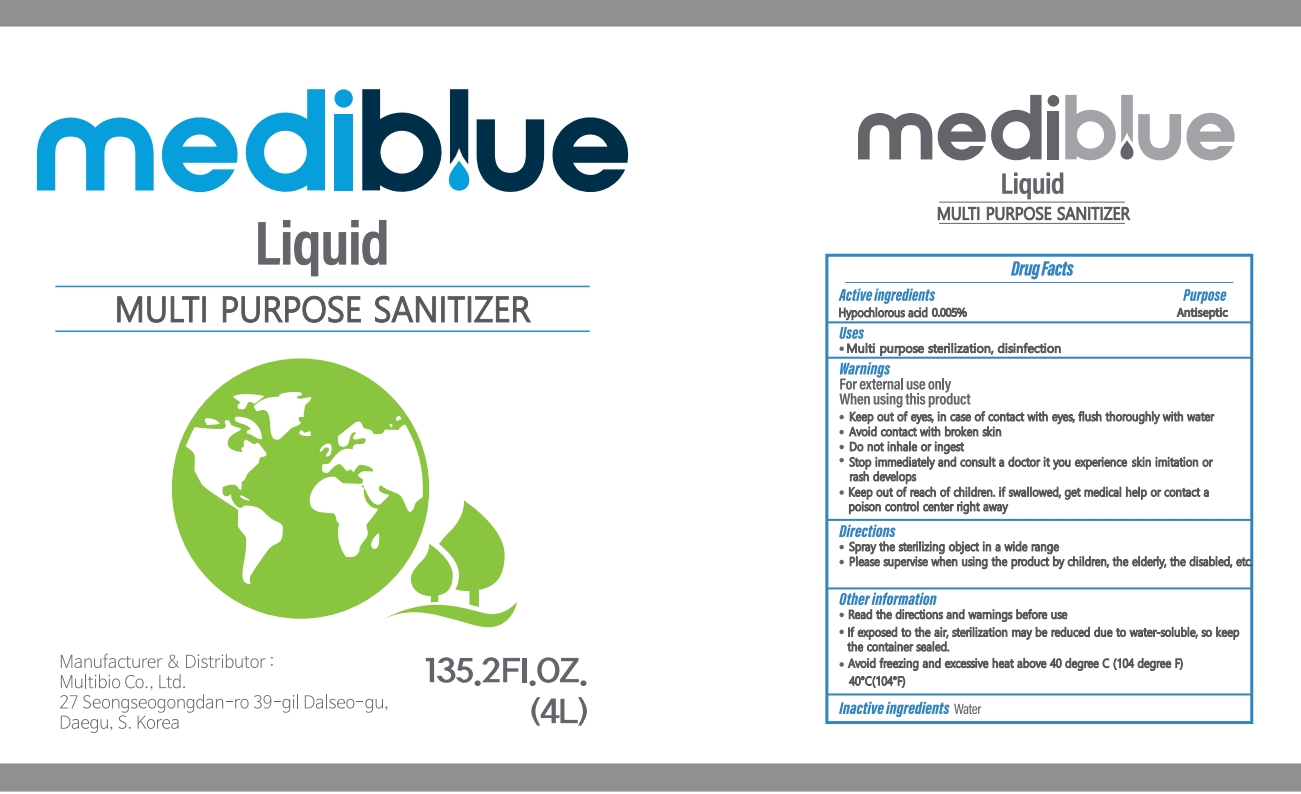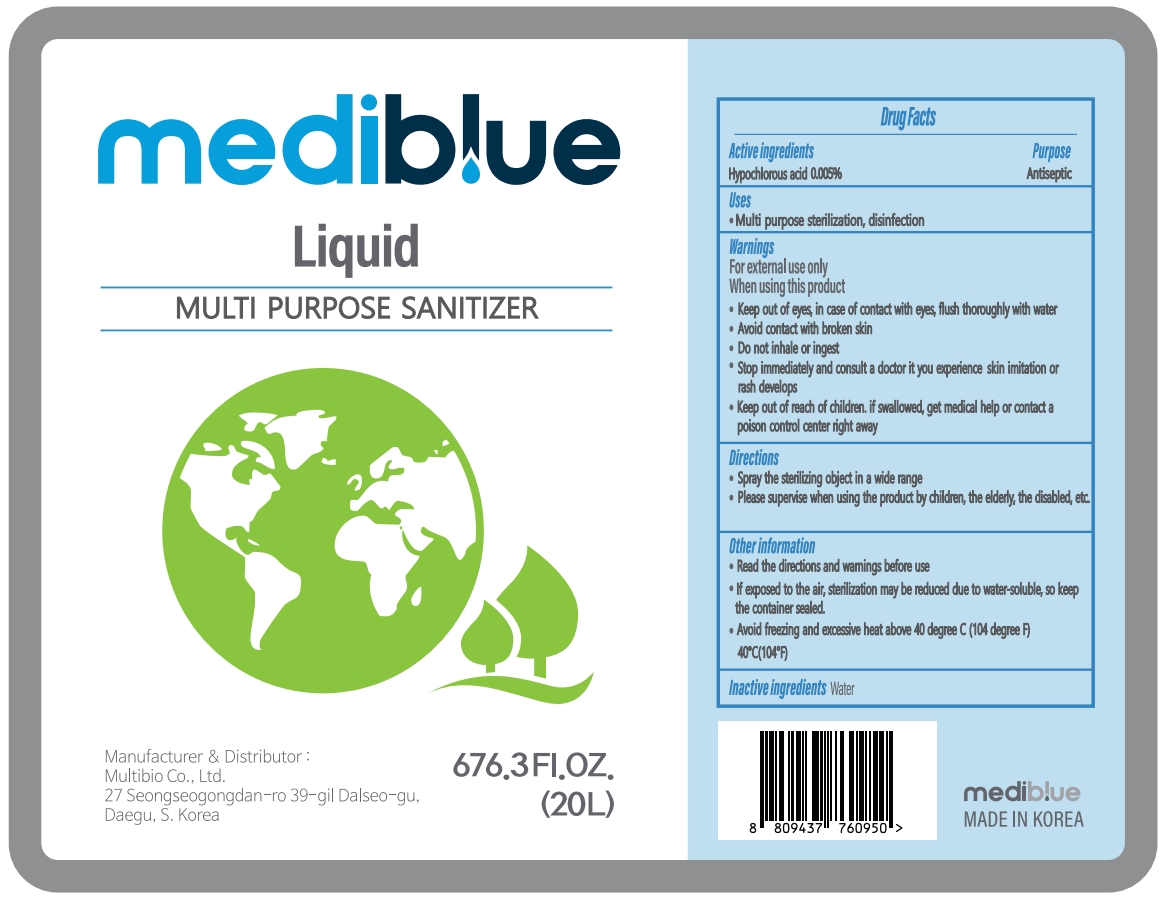 DRUG LABEL: MEDIBLUE
NDC: 76847-301 | Form: LIQUID
Manufacturer: Multibio Co., Ltd
Category: otc | Type: HUMAN OTC DRUG LABEL
Date: 20220218

ACTIVE INGREDIENTS: HYPOCHLOROUS ACID 0.005 g/100 mL
INACTIVE INGREDIENTS: WATER 99.995 mL/100 mL

76847-301 Mediblue

ACTIVE INGREDIENT

Hypochlorous acid 0.005%

PURPOSE

Antiseptic

USES

Multi purpose sterilization, disinfection

WARNINGS

For external use only

WHEN USING THIS PRODUCT

Keep out of eyes, in case of contact with eyes, flush thoroughly with water

Avoid contact with broken skin

Do not inhale or ingest

WHEN USING THIS PRODUCT

Stop immediately and consult a doctor it you experience skin imitation or rash develops

WHEN USING THIS PRODUCT

Keep out of reach of children. if swallowed, get medical help or contact a posion control center right away.

DIRECTIONS

Spray the sterilizing object in a wide range

Please supervise when using the product by children, the elderly, the disabled, etc.

OTHER INFORMATION

Read the directions and warnings before use

If exposed to the air, sterilization may be reduced due to water-soluble, so keep the container sealed.

Avoid freezing and excessive heat above 40 degree C (104 degree F) 40C(104F)

INACTIVE INGREDIENTS

Water